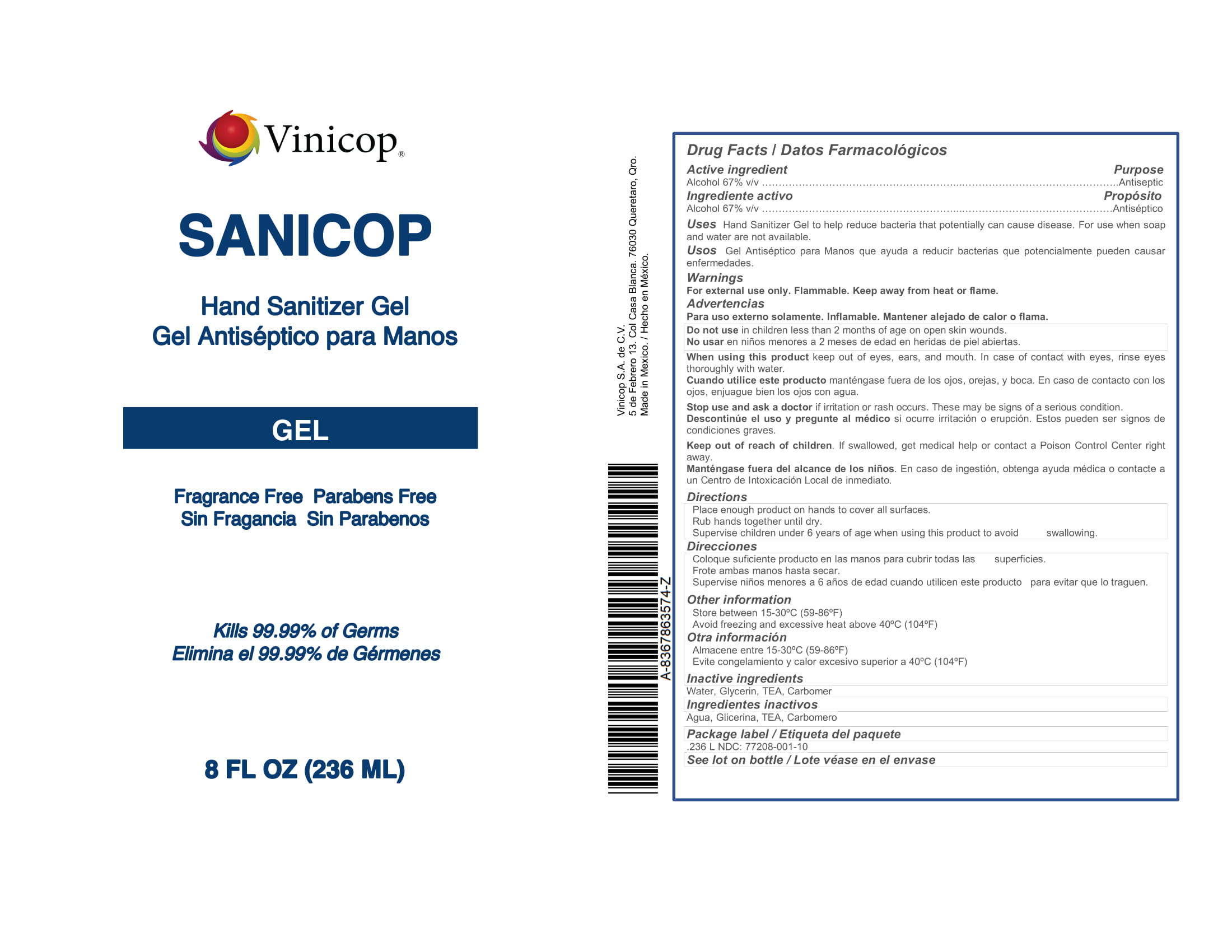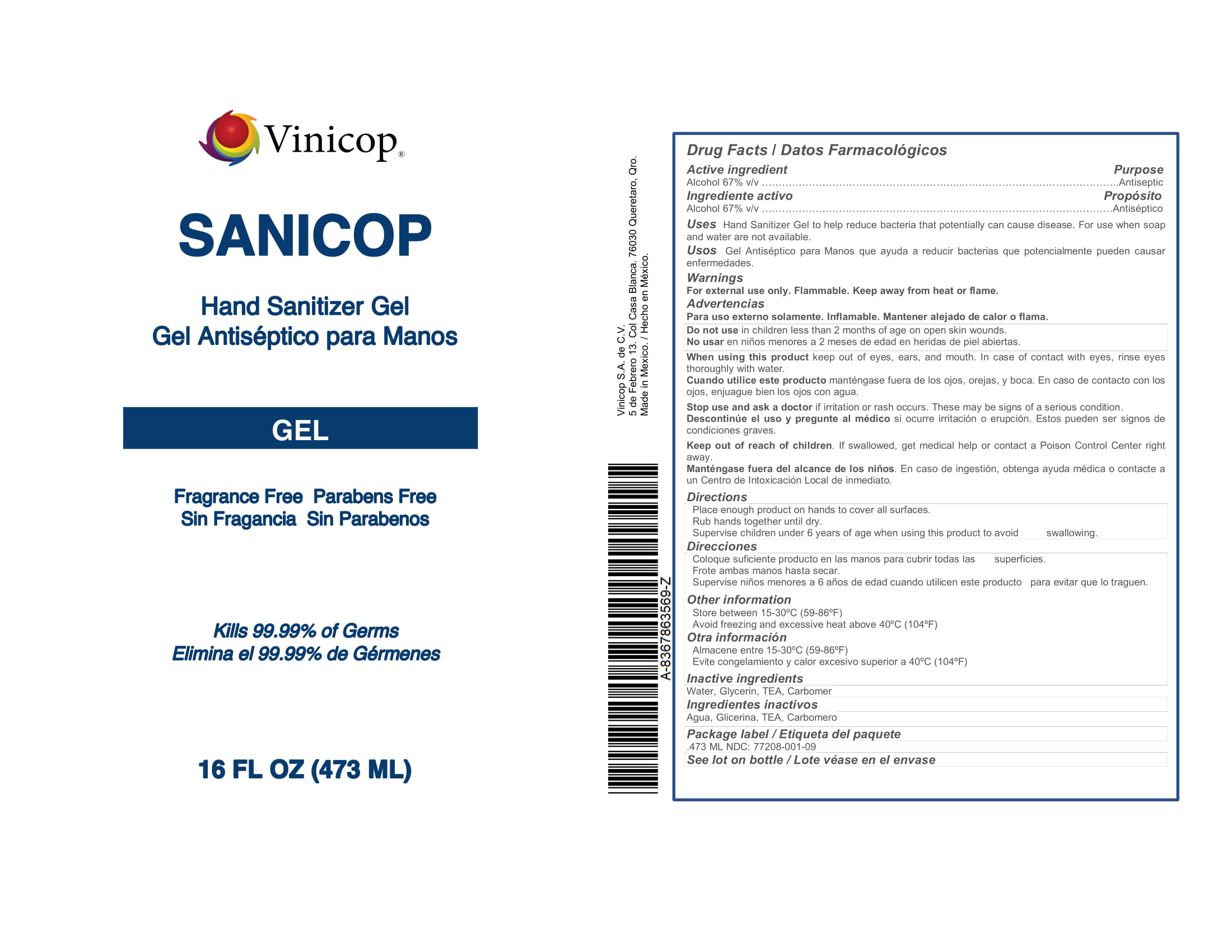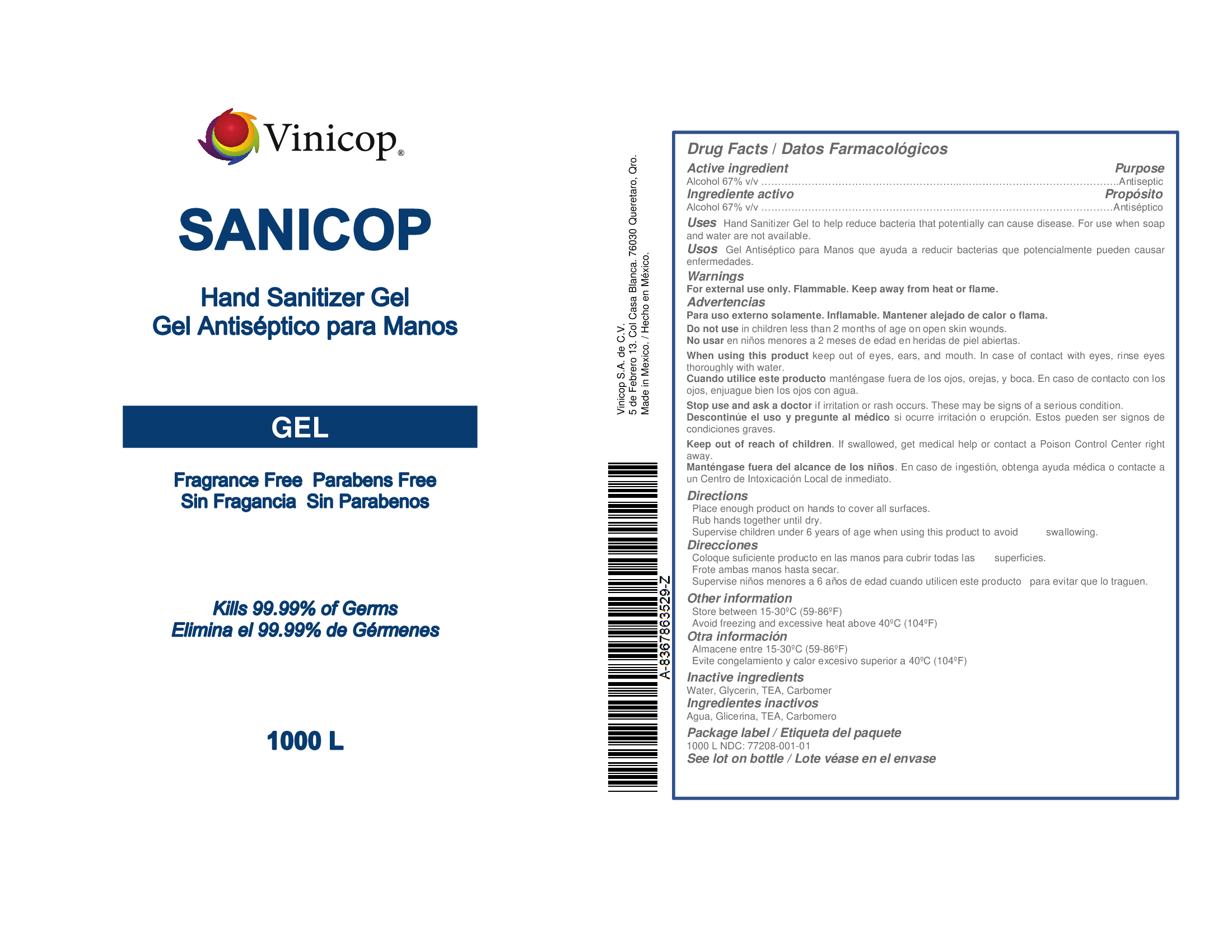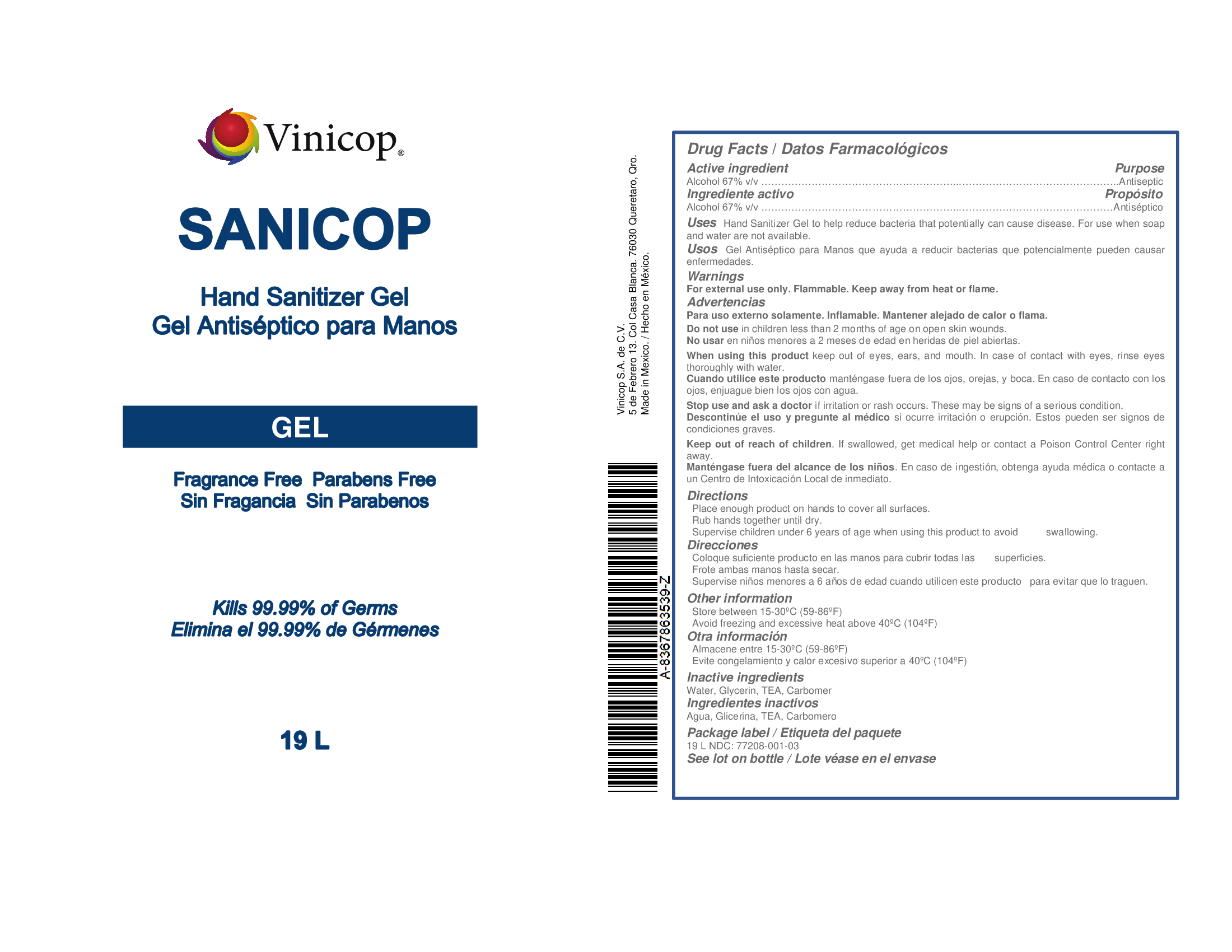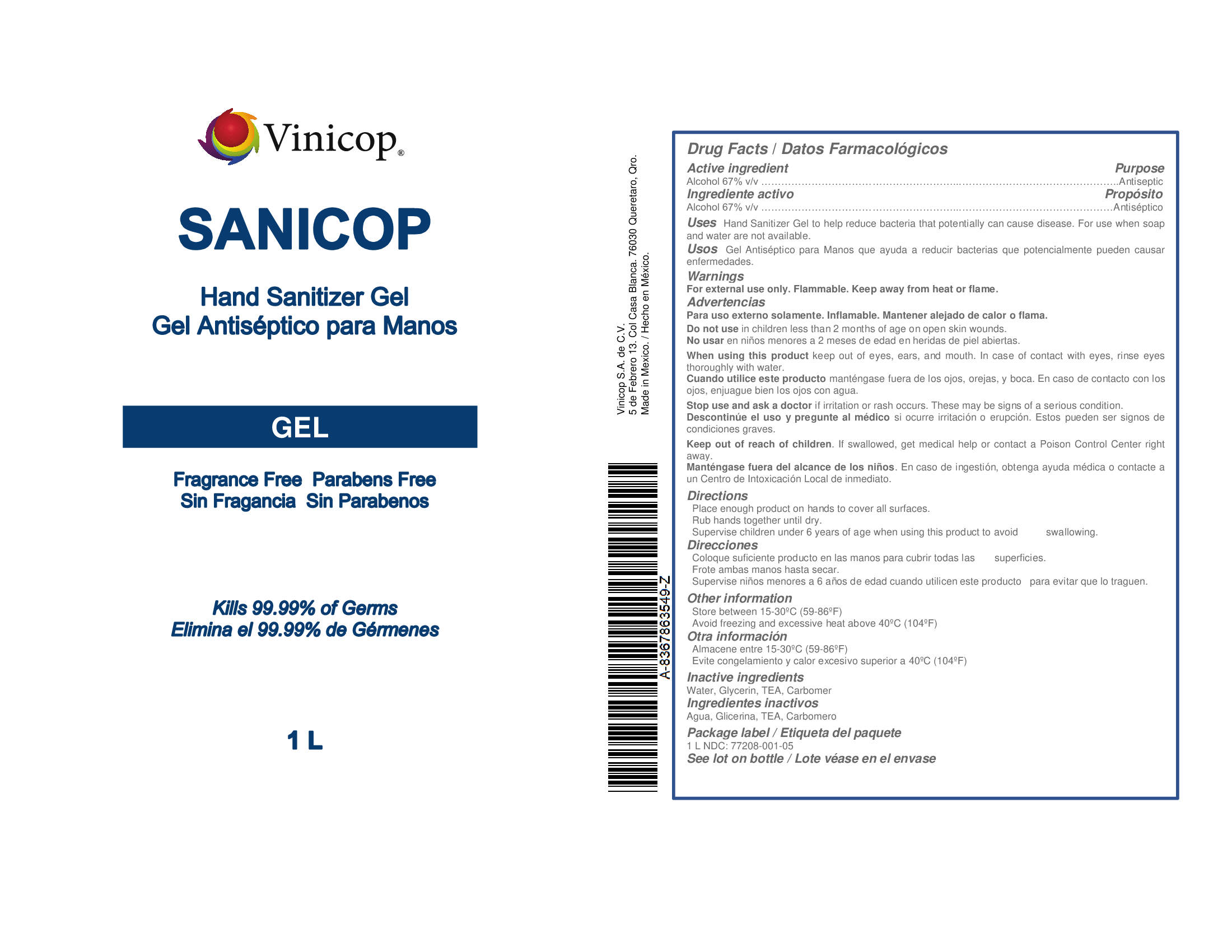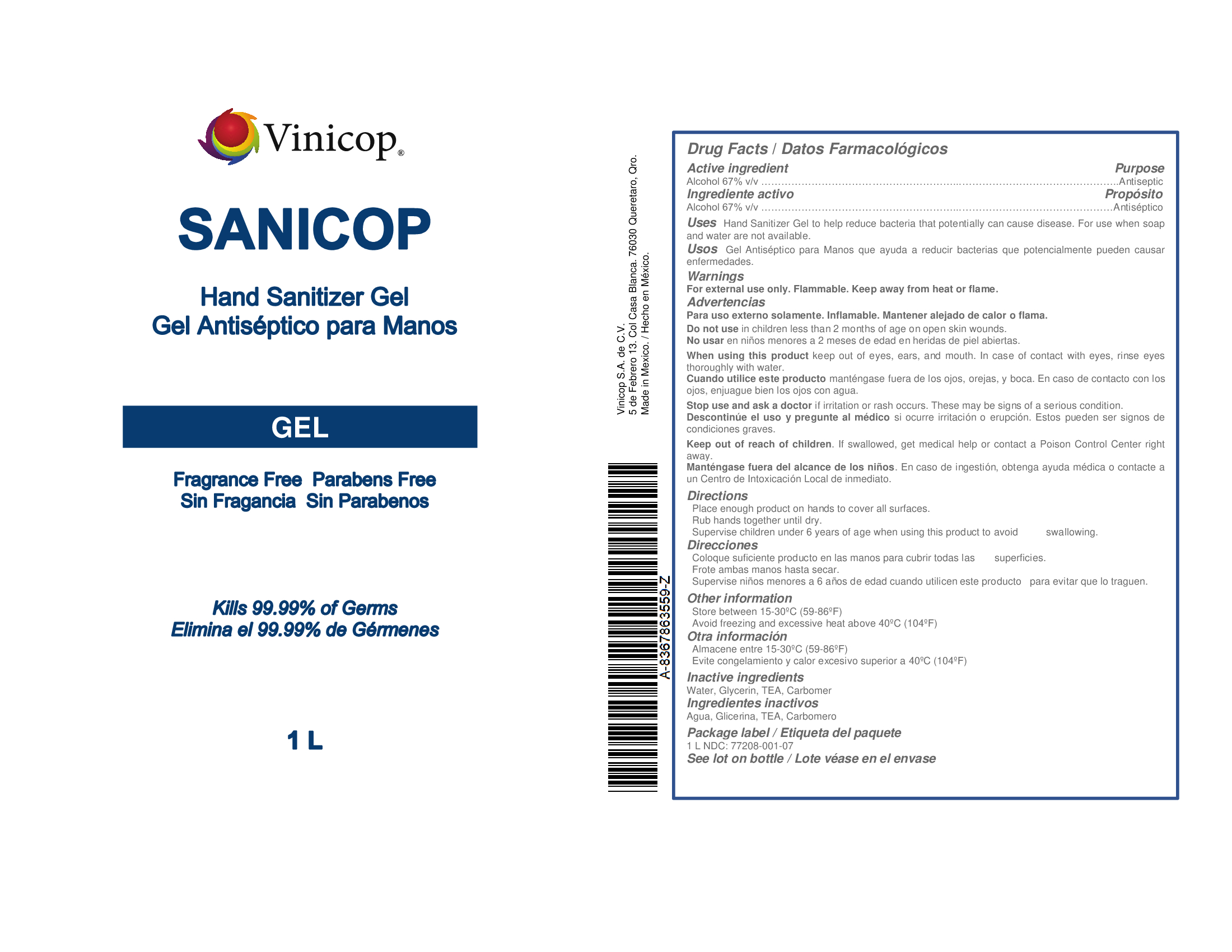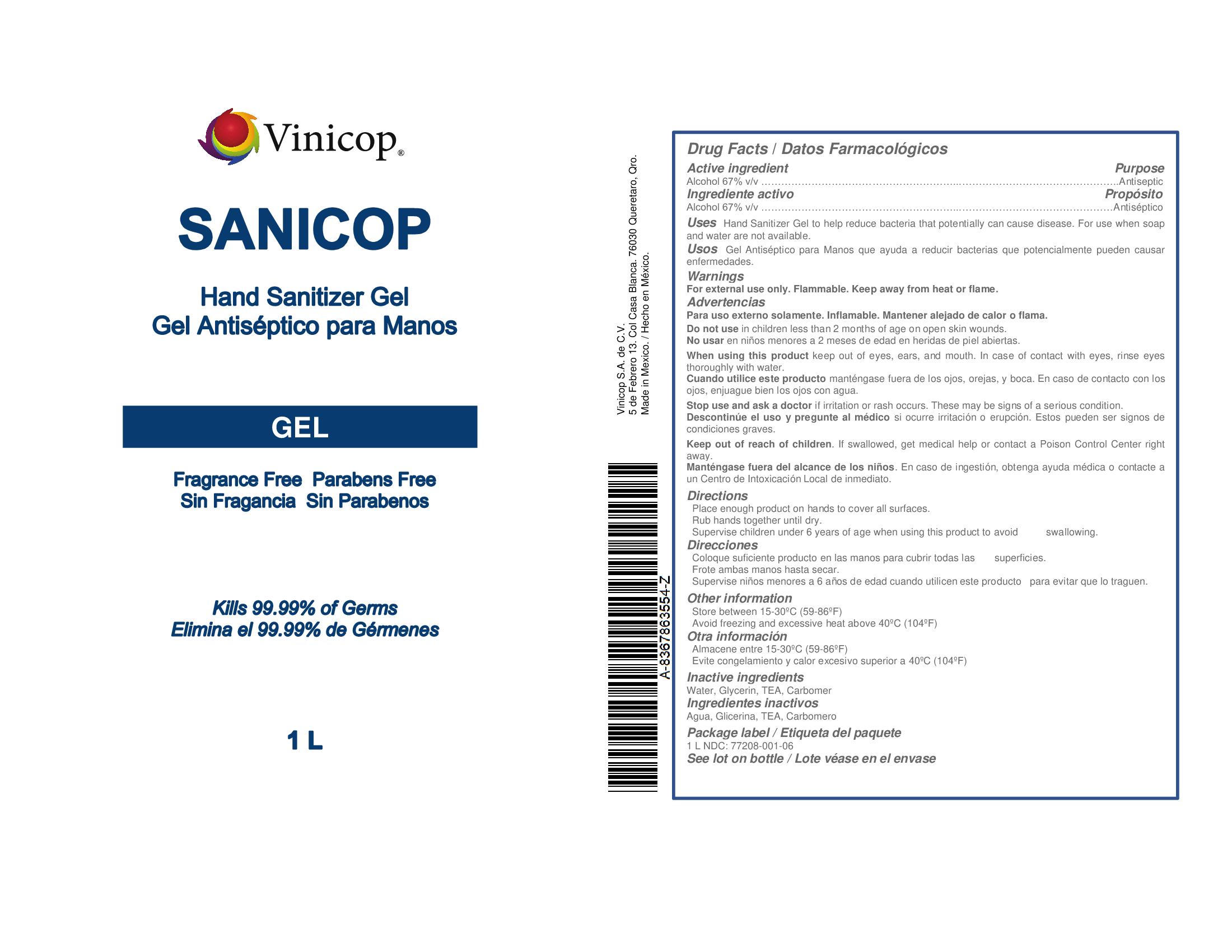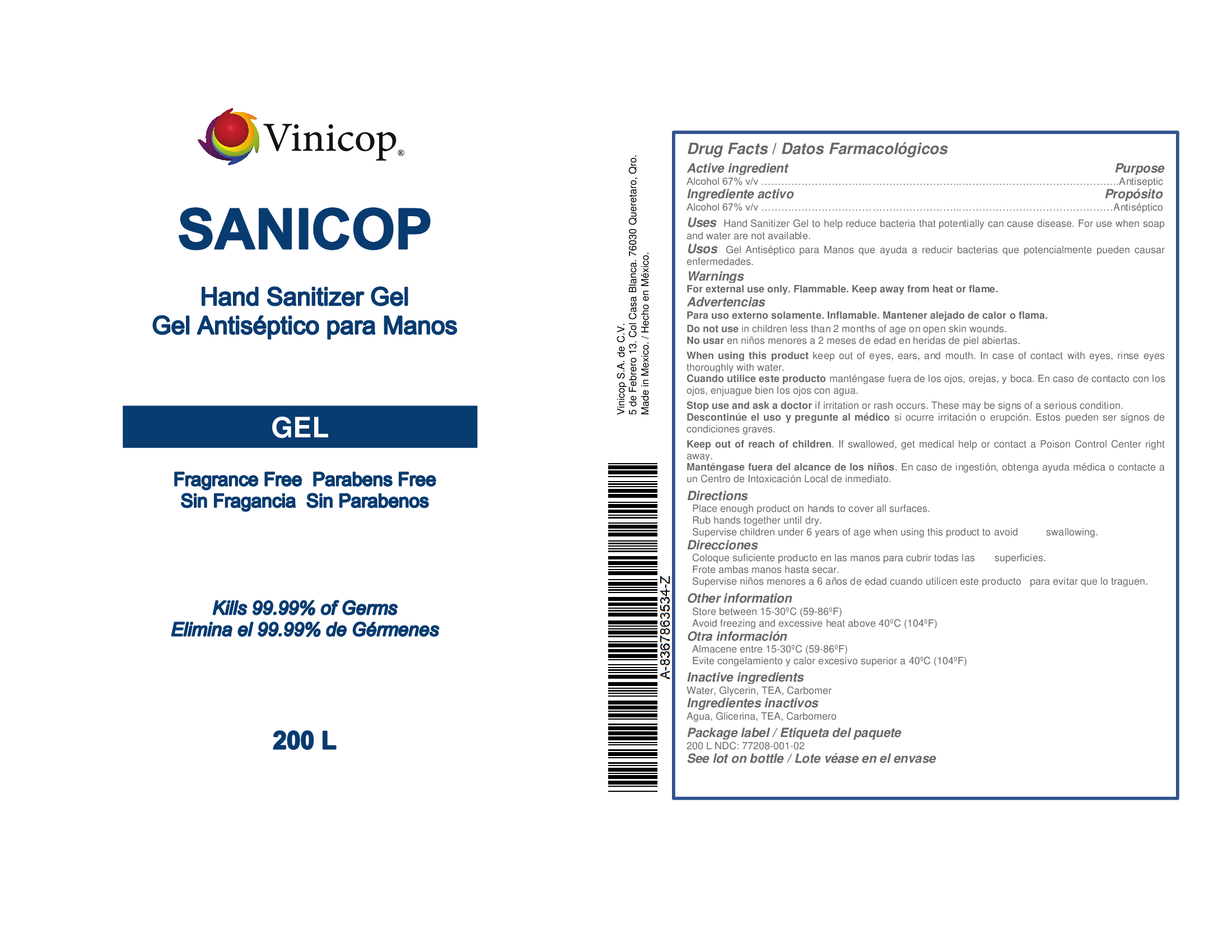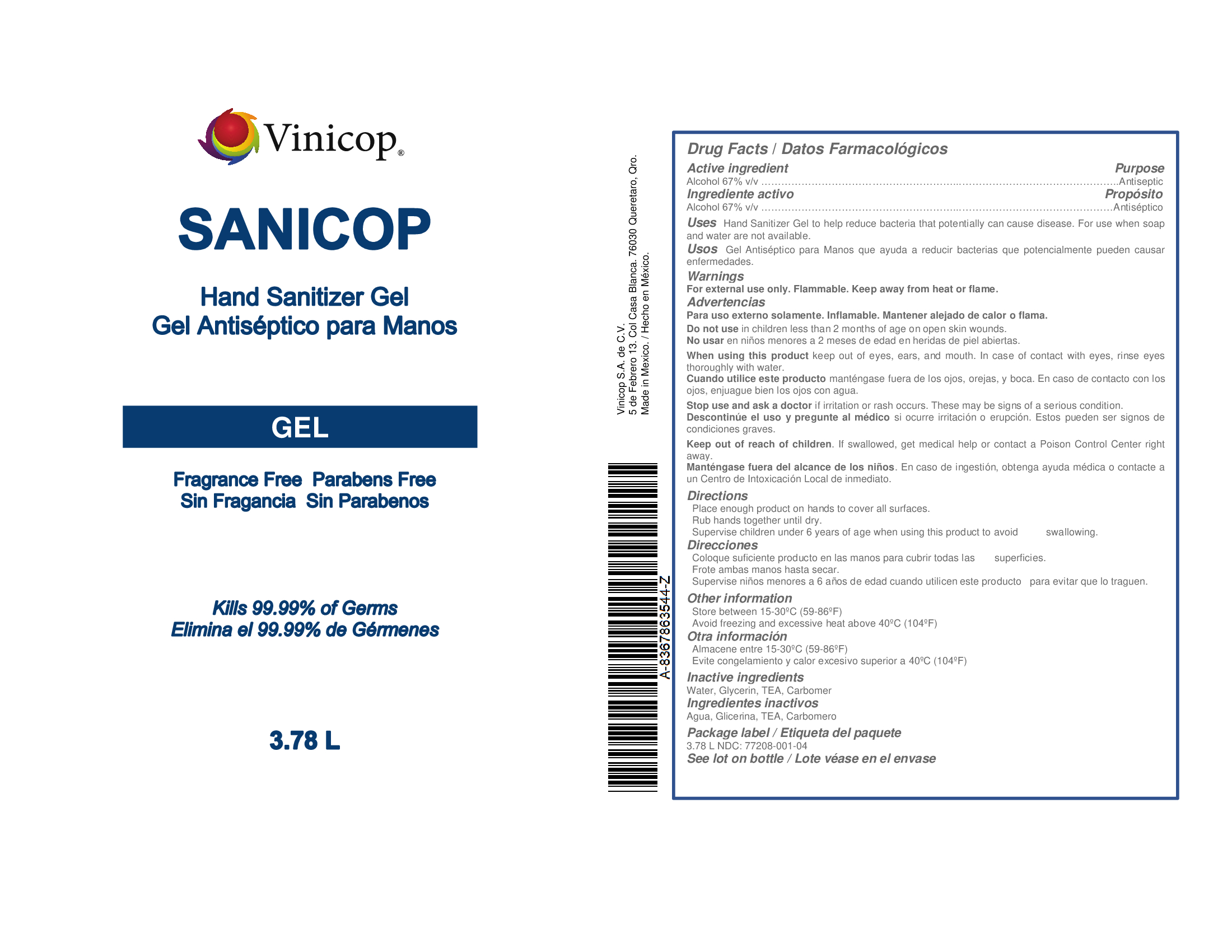 DRUG LABEL: SANICOP
NDC: 77208-001 | Form: GEL
Manufacturer: vinicop s.a. de c.v.
Category: otc | Type: HUMAN OTC DRUG LABEL
Date: 20200520

ACTIVE INGREDIENTS: ALCOHOL 67 mL/100 mL
INACTIVE INGREDIENTS: POLYACRYLIC ACID (8000 MW); TROLAMINE; GLYCERIN; WATER

Active ingredients

Alcohol 67% v/v. Purpose: Antiseptic

Purpose

Antiseptic, Hand Sanitizer

Use

Hand Sanitizer to help reduce bacteria that potentially can cause disease. For use when soap and water are not available.

Warnings

For external use only. Flammable. Keep away from heat or flame

Do not use:

· in children less than 2 months of age

· on open skin wounds

When using this product keep out of eyes, ears, and mouth. In case of contact with eyes, rinse eyes thoroughly with water.

Stop use and ask a doctor if irritation or rash occurs. These may be signs of a serious condition.

Keep out of reach of children. If swallowed, get medical help or contact a Poison Control Center right away.

Directions

· Place enough product on hands to cover all surfaces. Rub hands together until dry.

· Supervise children under 6 years of age when using this product to avoid swallowing.

Other information

· Store between 15-30ºC (59-86ºF)

· Avoid freezing and excessive heat above 40ºC (104ºF)

Inactive ingredients

Glyceryn, Water, TEA, Carbomer

PACKAGE LABEL

.473 L NDC: 77208-001-09

.236L NDC: 77208-001-10

1L NDC: 77208-001-05

1L NDC: 77208-001-07

1L NDC: 77208-001-06

3.78L NDC: 77208-001-04

19L NDC: 77208-001-03

200L NDC: 77208-001-02

1000L NDC: 77208-001-01